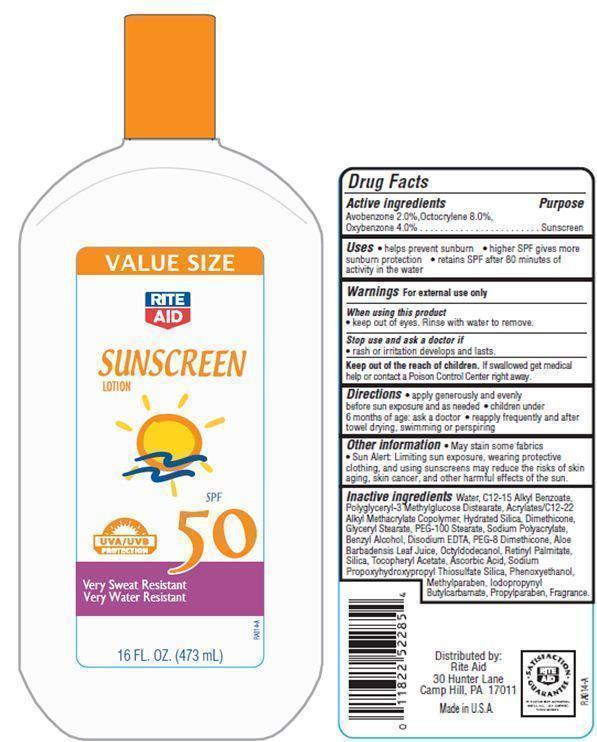 DRUG LABEL: Rite Aid Sport Sunscreen
                
NDC: 11822-9015 | Form: LOTION
Manufacturer: RITE AID CORPORATION
Category: otc | Type: HUMAN OTC DRUG LABEL
Date: 20121207

ACTIVE INGREDIENTS: AVOBENZONE 2 g/100 g; OCTOCRYLENE 8 g/100 g; OXYBENZONE 4 g/100 g
INACTIVE INGREDIENTS: WATER; HYDRATED SILICA; DIMETHICONE; GLYCERYL MONOSTEARATE; PEG-100 STEARATE; BENZYL ALCOHOL; EDETATE DISODIUM; ALOE VERA LEAF; OCTYLDODECANOL; VITAMIN A PALMITATE; SILICON DIOXIDE; .ALPHA.-TOCOPHEROL ACETATE; ASCORBIC ACID; PHENOXYETHANOL; METHYLPARABEN; PROPYLPARABEN

Drug Facts

Active Ingredients

Avobenzone 2.0%
Octocrylene 8.0%
Oxybenzone 4.0%

Purpose

Sunscreen

Uses

- helps prevent sunburn
- higher SPF gives more sunburn protection
- retains SPF after 80 minutes of activity in the water

Warnings

For external use only

When using this product

- keep out of eyes.Rinse with water to remove.

Stop use and ask a doctor if

rash or irritation develops and lasts.

Keep out of the reach of children.

If swallowed get medical help or contact a Poison Control Center right away.

Directions

- apply generously and evenly before sun exposure and as needed
- Children under 6 months of age:ask a doctor
- reapply after towel drying, swimming or perspiring

Other Information

- May stain some fabrics
- Sun Alert: Limiting sun exposure, wearing protective clothing, and using sunscreens may reduce the risks of skin aging, skin cancer, and other harmful effects of the sun.

Inactive Ingredients

Water, C12-15 Alkyl Benzoate, Polyglyceryl-3 Methylglucose Distearate, Acrylates/C12-22 Alkyl Methacrylate Copolymer, Hydrated Silica, Glyceryl Stearate, Dimethicone, PEG-100 Stearate, Sodium Polyacrylate, Benzyl Alcohol, Disodium EDTA, PEG-4 Dilaurate, PEG-4 Laurate, PEG-4, PEG-8 Dimethicone, Aloe Barbadensis Leaf Juice Powder, Octyldodecanol, Retinyl Palmitate, Silica, Tocopheryl Acetate, Ascorbic Acid, Sodium Propoxyhydroxypropyl Thiosulfate Silica, Phenoxyethanol, Methylparaben, Propylparaben, Iodopropynyl Butylcarbamate, Fragrance.

Principal Display Panel

VALUE SIZE
RITE AID
SUNSCREEN LOTION
SPF 50
UVA/UVB PROTECTION
Very Sweat Resistant
Very Water Resistant
16 FL OZ(473 mL)